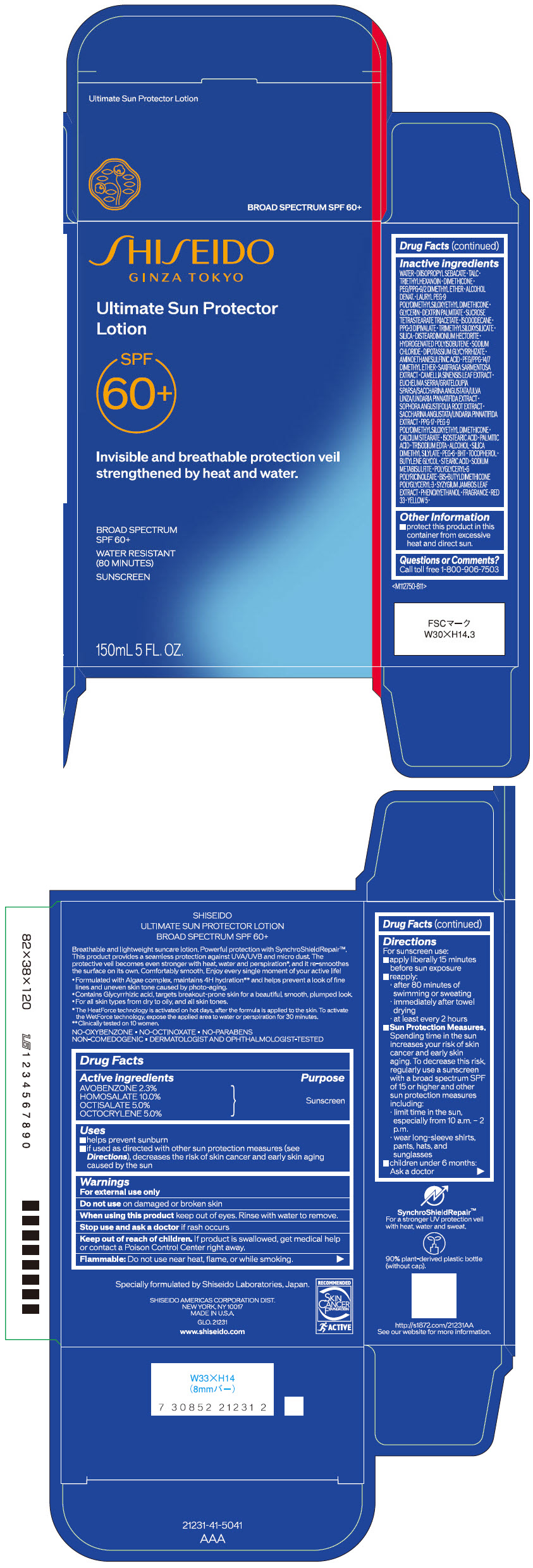 DRUG LABEL: SHISEIDO ULTIMATE SUN PROTECTOR
NDC: 58411-888 | Form: LOTION
Manufacturer: SHISEIDO AMERICAS CORPORATION
Category: otc | Type: HUMAN OTC DRUG LABEL
Date: 20250321

ACTIVE INGREDIENTS: AVOBENZONE 3.67425 g/150 mL; HOMOSALATE 7.9875 g/150 mL; OCTISALATE 7.9875 g/150 mL; OCTOCRYLENE 7.9875 g/150 mL
INACTIVE INGREDIENTS: WATER; DIISOPROPYL SEBACATE; TALC; TRIETHYLHEXANOIN; DIMETHICONE; PEG/PPG-9/2 DIMETHYL ETHER; ALCOHOL; LAURYL PEG-9 POLYDIMETHYLSILOXYETHYL DIMETHICONE; GLYCERIN; DEXTRIN PALMITATE (CORN; 20000 MW); ISODODECANE; SUCROSE TETRASTEARATE TRIACETATE; TRIMETHYLSILOXYSILICATE (M/Q 0.6-0.8); SILICON DIOXIDE; DISTEARDIMONIUM HECTORITE; HYDROGENATED POLYISOBUTENE (1300 MW); PPG-17; PEG-9 POLYDIMETHYLSILOXYETHYL DIMETHICONE; CALCIUM STEARATE; PHENOXYETHANOL; ISOSTEARIC ACID; PALMITIC ACID; EDETATE TRISODIUM; POLYETHYLENE GLYCOL 300; SILICA DIMETHYL SILYLATE; SODIUM CHLORIDE; BUTYLATED HYDROXYTOLUENE; .ALPHA.-TOCOPHEROL; GLYCYRRHIZINATE DIPOTASSIUM; BUTYLENE GLYCOL; PEG/PPG-14/7 DIMETHYL ETHER; POLYGLYCERYL-6 POLYRICINOLEATE; SODIUM METABISULFITE; STEARIC ACID; SAXIFRAGA STOLONIFERA LEAF; GREEN TEA LEAF; SYZYGIUM JAMBOS LEAF; FD&C YELLOW NO. 5; D&C RED NO. 33; SOPHORA FLAVESCENS ROOT

SHISEIDO ULTIMATE SUN PROTECTOR LOTION

Drug Facts

ACTIVE INGREDIENT

Active ingredients | Purpose
AVOBENZONE 2.3% | Sunscreen
HOMOSALATE 10.0% | Sunscreen
OCTISALATE 5.0% | Sunscreen
OCTOCRYLENE 5.0% | Sunscreen

Uses

- helps prevent sunburn
- if used as directed with other sun protection measures (see Directions), decreases the risk of skin cancer and early skin aging caused by the sun

Warnings

For external use only

Do not use on damaged or broken skin

When using this product keep out of eyes. Rinse with water to remove.

Stop use and ask a doctor if rash occurs.

Keep out of reach of children. If product is swallowed, get medical help or contact a Poison Control Center right away.

Flammable

Do not use near heat, flame, or while smoking

Directions

For sunscreen use:

- apply liberally 15 minutes before sun exposure
- reapply:
  - after 80 minutes of swimming or sweating
  - immediately after towel drying
  - at least every 2 hours
- Sun Protection Measures. Spending time in the sun increases your risk of skin cancer and early skin aging. To decrease this risk, regularly use a sunscreen with a Broad Spectrum SPF of 15 or higher and other sun protection measures including:
  - limit time in the sun, especially from 10 a.m. – 2 p.m.
  - wear long-sleeve shirts, pants, hats, and sunglasses
- children under 6 months: Ask a doctor

Inactive Ingredients

WATER･DIISOPROPYL SEBACATE･TALC･TRIETHYLHEXANOIN･DIMETHICONE･PEG/PPG-9/2 DIMETHYL ETHER･ALCOHOL DENAT.･LAURYL PEG-9 POLYDIMETHYLSILOXYETHYL DIMETHICONE･GLYCERIN･DEXTRIN PALMITATE･SUCROSE TETRASTEARATE TRIACETATE･ISODODECANE･PPG-3 DIPIVALATE･TRIMETHYLSILOXYSILICATE･SILICA･DISTEARDIMONIUM HECTORITE･HYDROGENATED POLYISOBUTENE･SODIUM CHLORIDE･DIPOTASSIUM GLYCYRRHIZATE･AMINOETHANESULFINIC ACID･PEG/PPG-14/7 DIMETHYL ETHER･SAXIFRAGA SARMENTOSA EXTRACT･CAMELLIA SINENSIS LEAF EXTRACT･EUCHEUMA SERRA/GRATELOUPIA SPARSA/SACCHARINA ANGUSTATA/ULVA LINZA/UNDARIA PINNATIFIDA EXTRACT･SOPHORA ANGUSTIFOLIA ROOT EXTRACT･SACCHARINA ANGUSTATA/UNDARIA PINNATIFIDA EXTRACT･PPG-17･PEG-9 POLYDIMETHYLSILOXYETHYL DIMETHICONE･CALCIUM STEARATE･ISOSTEARIC ACID･PALMITIC ACID･TRISODIUM EDTA･ALCOHOL･SILICA DIMETHYL SILYLATE･PEG-6･BHT･TOCOPHEROL･BUTYLENE GLYCOL･STEARIC ACID･SODIUM METABISULFITE･POLYGLYCERYL-6 POLYRICINOLEATE･BIS-BUTYLDIMETHICONE POLYGLYCERYL-3･SYZYGIUM JAMBOS LEAF EXTRACT･PHENOXYETHANOL･FRAGRANCE･RED 33･YELLOW 5･

Other information

- protect this product in this container from excessive heat and direct sun.

Questions or comments?

Call toll free 1-800-906-7503

PRINCIPAL DISPLAY PANEL - 150 mL Container Carton

SHISEIDO
GINZA TOKYO

Ultimate Sun Protector
Lotion

SPF
60+

Invisible and breathable protection veil
strengthened by heat and water.

BROAD SPECTRUM
SPF 60+

WATER RESISTANT
(80 MINUTES)

SUNSCREEN

150mL 5 FL. OZ.